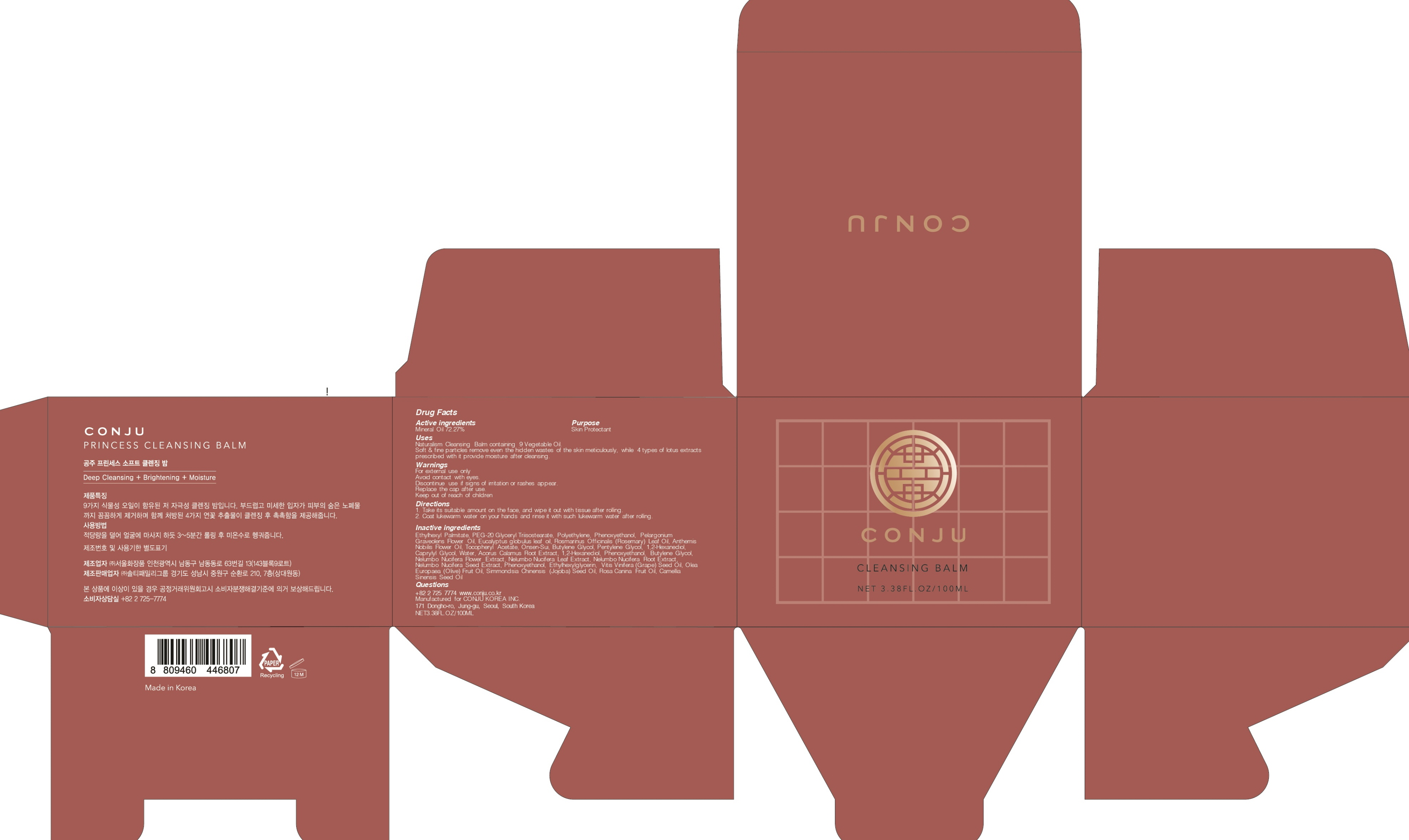 DRUG LABEL: CONJU PRINCESS CLEANSING BALM
NDC: 72950-020 | Form: GEL
Manufacturer: Conju Korea Inc.
Category: otc | Type: HUMAN OTC DRUG LABEL
Date: 20190318

ACTIVE INGREDIENTS: Mineral Oil 72.27 g/100 mL
INACTIVE INGREDIENTS: Ethylhexyl Palmitate; Phenoxyethanol

ACTIVE INGREDIENT

Active ingredient: Mineral Oil 72.27%

INACTIVE INGREDIENT

Inactive ingredients:

Ethylhexyl Palmitate, PEG-20 Glyceryl Triisostearate, Polyethylene, Phenoxyethanol, Pelargonium Graveolens Flower Oil, Eucalyptus globulus leaf oil, Rosmarinus Officinalis (Rosemary) Leaf Oil, Anthemis Nobilis Flower Oil, Tocopheryl Acetate, Onsen-Sui, Butylene Glycol, Pentylene Glycol, 1,2-Hexanediol, Caprylyl Glycol, Water, Acorus Calamus Root Extract, 1,2-Hexanediol, Phenoxyethanol, Butylene Glycol, Nelumbo Nucifera Flower Extract, Nelumbo Nucifera Leaf Extract, Nelumbo Nucifera Root Extract, Nelumbo Nucifera Seed Extract, Phenoxyethanol, Ethylhexylglycerin, Vitis Vinifera (Grape) Seed Oil, Olea Europaea (Olive) Fruit Oil, Simmondsia Chinensis (Jojoba) Seed Oil, Rosa Canina Fruit Oil, Camellia Sinensis Seed Oil

PURPOSE

Purpose: Skin Protectant

WARNINGS

For external use only
Avoid contact with eyes.
Discontinue use if signs of irritation or rashes appear.
Replace the cap after use.
Keep out of reach of children

KEEP OUT OF REACH OF CHILDREN

Uses

Naturalism Cleansing Balm containing 9 Vegetable Oil.
Soft & fine particles remove even the hidden wastes of the skin meticulously, while 4 types of lotus extracts prescribed with it provide moisture after cleansing.

Directions

1. Take its suitable amount on the face, and wipe it out with tissue after rolling.
2. Coat lukewarm water on your hands and rinse it with such lukewarm water after rolling.